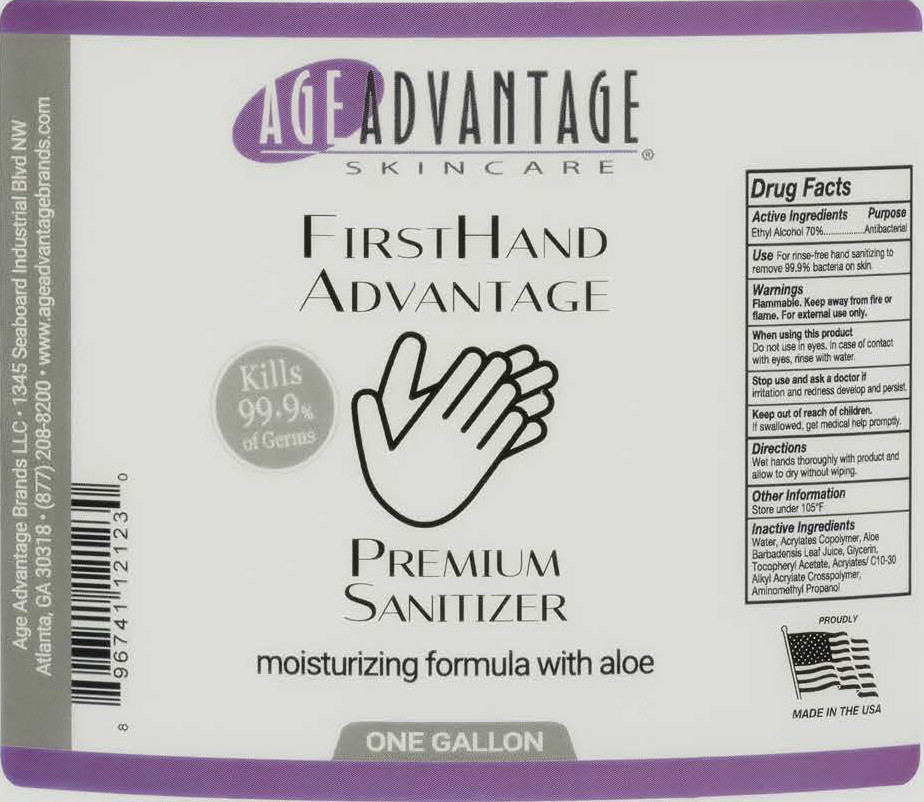 DRUG LABEL: FirstHand Advantage Premium Sanitizer
NDC: 79215-101 | Form: GEL
Manufacturer: Age Advantage Brands LLC
Category: otc | Type: HUMAN OTC DRUG LABEL
Date: 20200514

ACTIVE INGREDIENTS: Alcohol 70 mL/100 mL
INACTIVE INGREDIENTS: Water; Butyl Acrylate/Methyl Methacrylate/Methacrylic Acid Copolymer (18000 MW); Aloe Vera Leaf; Glycerin; .Alpha.-Tocopherol Acetate; Carbomer Interpolymer Type A (Allyl Sucrose Crosslinked); Aminomethylpropanol

Hand Sanitizer

Drug Facts:

Active Ingredients:

Ethyl Alcohol 70%

Purpose

Antibacterial

USE:

Hand sanitizer to help reduce bacteria that potentially can cause disease. For use when soap and water are not available.

WARNINGS:

For external use only

Keep out of reach of Children

If swallowed, get medical help or contact a poison control center immediately

When using this product keep out of eyes, ears, and mouth. In case of contact with eyes, rinse eyes thoroughly with water.

Stop use and ask a doctor if irritation or rash occurs. These may be signs of a serious condition.

DIRECTIONS:

Place enough product on hands to cover all surfaces. Rub hands together until dry. • Supervise children under 6 years of age when using this product to avoid swallowing.

OTHER INFORMATION:

Store between 15- 30C (59- 86F) • Avoid freezing and excessive heat above 40C (104F)

INACTIVE INGREDIENTS:

Water, Acrylates Copolymer, Aloe Barbadensis Leaf Juice, Glycerin, Tocopheryl Acetate (Vitamin E), Acrylates/C10-30 Alkyl Acrylate Crosspolmer, Aminomethyl Propanol.

Principal Display Panel – 1 Gallon Bottle Label

AGE ADVANTAGE®

SKIN CARE

FIRST HAND
ADVANTAGE

Kills 99.9%
of Germs

PREMIUM
SANITIZER

moisturizing formula with aloe

ONE GALLON